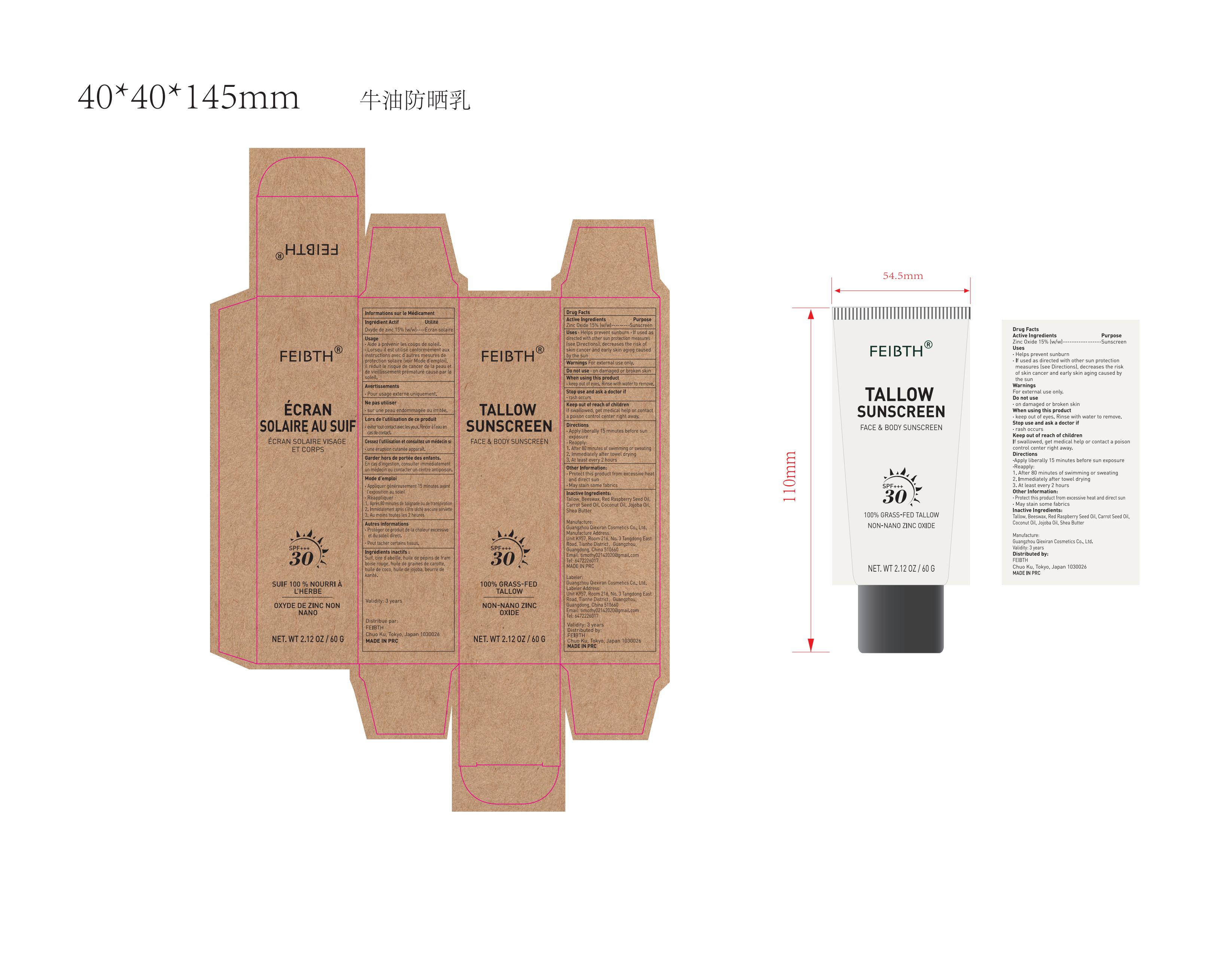 DRUG LABEL: FEIBTH TALLOW SUNSCREEN
NDC: 85817-002 | Form: CREAM
Manufacturer: Guangzhou Qiexiran Cosmetics Co., Ltd.
Category: otc | Type: HUMAN OTC DRUG LABEL
Date: 20250619

ACTIVE INGREDIENTS: ZINC OXIDE 15 g/100 g
INACTIVE INGREDIENTS: RASPBERRY; COCONUT OIL; TALLOW; JOJOBA OIL; BEESWAX; SHEA BUTTER; CARROT SEED OIL

85817-002

Active Ingredient

Zinc Oxide 15% (w/w)

Purpose

Sunscreen

Use

· Helps prevent sunburn
· If used as directed with other sun protection measures (see Directions), decreases the risk of skin cancer and early skin aging caused by the sun

Warnings

For external use only.

Do not use

· on damaged or broken skin

When Using

· keep out of eyes. Rinse with water to remove.

Stop Use

· rash occurs

Ask Doctor

· rash occurs

Keep Out Of Reach Of Children

If swallowed, get medical help or contact a poison control center right away.

Directions

·Apply liberally 15 minutes before sun exposure
·Reapply:
1.After 80 minutes of swimming or sweating
2.Immediately after towel drying
3.At least every 2 hours

Other information

· Protect this product from excessive heat and direct sun
· May stain some fabrics

Inactive ingredients

Tallow, Beeswax, Red Raspberry Seed Oil, Carrot Seed Oil, Coconut Oil, Jojoba Oil, Shea Butter